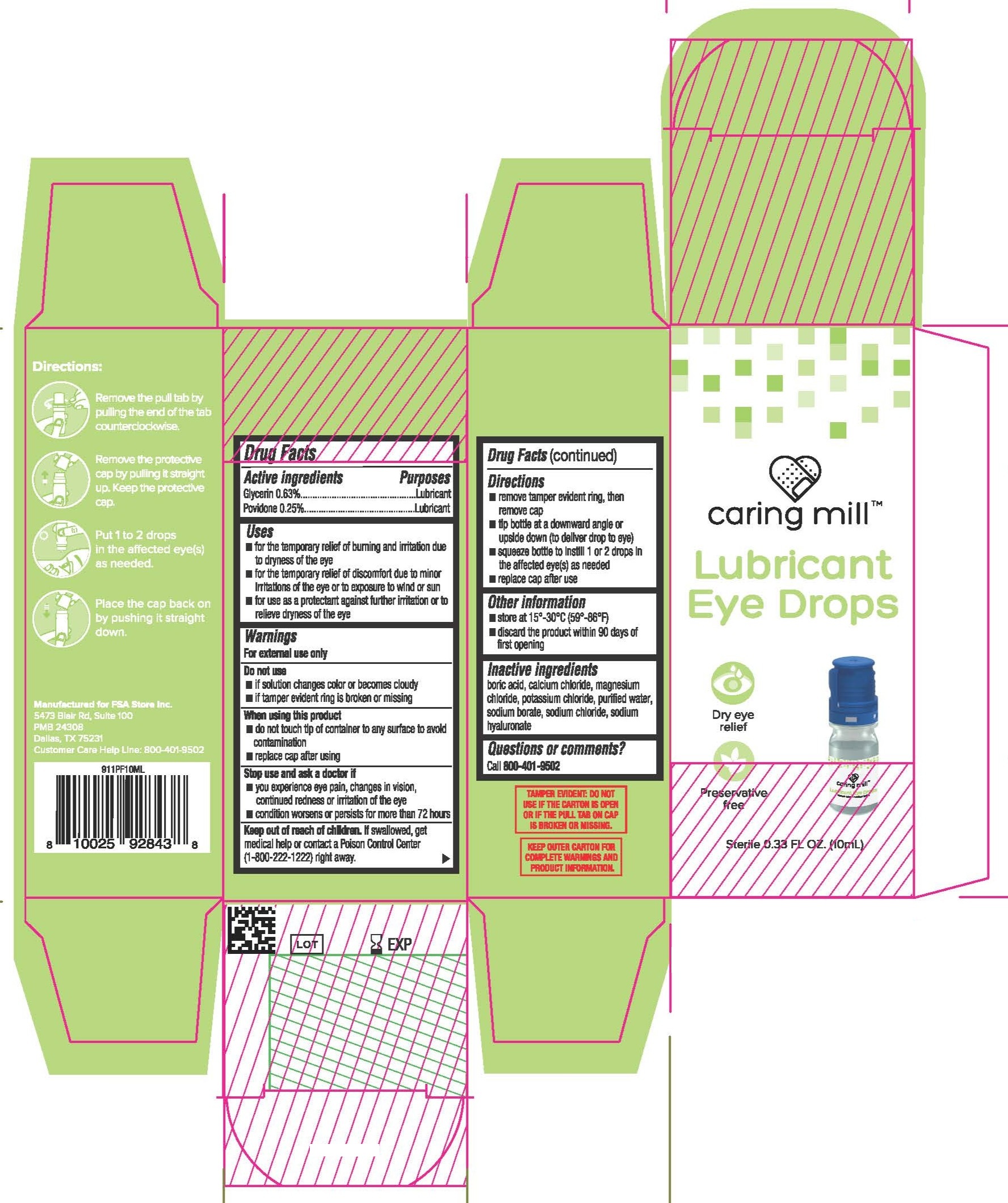 DRUG LABEL: Caring Mill Lubricant Eye Drops
NDC: 81522-911 | Form: SOLUTION/ DROPS
Manufacturer: FSA Store Inc
Category: otc | Type: HUMAN OTC DRUG LABEL
Date: 20250303

ACTIVE INGREDIENTS: GLYCERIN 0.63 g/100 mL; POVIDONE 0.25 g/100 mL
INACTIVE INGREDIENTS: CALCIUM CHLORIDE; MAGNESIUM CHLORIDE; SODIUM HYALURONATE; BORIC ACID; POTASSIUM CHLORIDE; SODIUM CHLORIDE; SODIUM BORATE

CARING MILL INITIAL LISTING

Active ingredients | Purposes
Glycerin 0.63% | Lubricant
Povidone 0.25% | Lubricant

INDICATIONS AND USAGE

Uses

- for the temporary relief of burning and irritation due to dryness of the eye
- for the temporary relief of discomfort due to minor irritations of the eye or to exposure to wind or sun
- for use as a protectant against further irritation or to relieve dryness of the eye

WARNINGS

For external use only

Do not use

- if solution changes color or becomes cloudy
- if tamper evident ring is broken or missing

Stop use and ask a doctor if

- you experence eye pain, changes in vision, continued redness or irritation of the eye
- condition worsens or persists for more than 72 hours

When using this product

- do not touch tip of container to nay surface to avoid contamination
- replace cap after using

Keep out of reach of children. If swallowed, get medical help or contact a Poison Control Center (1-800-222-1222) right away.

Directions

- remove tamper evident ring, then remove cap
- tip bottle at a downward angle or upside down (to deliver drop to eye)
- squeeze bottle to instill 1 or 2 drops in the affected eye(s) as needed
- replace cap after use

DOSAGE AND ADMINISTRATION

squeeze bottle to instill 1 or 2 drops in the affected eye(s) as needed

Other Information

- store at 15º-30ºC (59º-86ºF)
- discard the product within 90 days of first opening

Inactive ingredients

boric acid, calcium chloride, magnesium chloride, potassium chloride, purified water, sodium borate, sodium chloride, sodium hyaluronate

Questions or comments?

Call 800-401-9502

PACKAGE LABEL

caring mill

Lubricant Eye Drops

Dry eye relief

Preservative free

Sterile 0.33 FL OZ. (10mL)